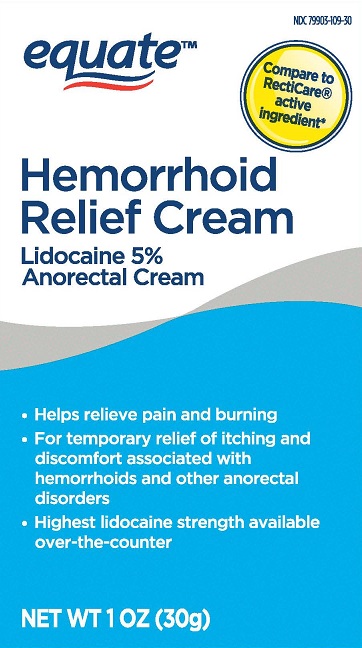 DRUG LABEL: EQUATE HEMORRHOID RELIEF
NDC: 79903-109 | Form: CREAM
Manufacturer: WALMART, INC
Category: otc | Type: HUMAN OTC DRUG LABEL
Date: 20251008

ACTIVE INGREDIENTS: LIDOCAINE 50 mg/1 g
INACTIVE INGREDIENTS: PROPYLENE GLYCOL; WATER; POLYSORBATE 80; TROLAMINE; HYDROGENATED SOYBEAN LECITHIN; BENZYL ALCOHOL; CARBOMER 940; ALPHA-TOCOPHEROL ACETATE; CHOLESTEROL; ISOPROPYL MYRISTATE

EQUATE HEMORRHOID RELIEF CREAM- LIDOCAINE 5%

ACTIVE INGREDIENT

Lidocaine 5% W/W

PURPOSE

Local Anesthetic

USES

helps relieve the pain, itching, and burning, associated with hemorrhoids and anorectal disorders.

WARNINGS

For external use only

When using this product

- use only as directed
- avoid contact with eyes
- do not exceed recommended dosage unless directed by a doctor
- do not put this product into the rectum by using fingers or any mechanical device or applicator

Stop use and ask a doctor if

- rectal bleeding occurs
- condition worsens or does not improve within 7 days
- symptoms clear up and occur again within a few days
- an allergic reaction develops to ingredients in this product
- symptom being treated does not subside or if redness, irritation, swelling, pain or other symptoms develop or increase

If pregnant or breast-feeding,

ask a health professional before use.

Keep out of reach of children and pets.

If swallowed, get medical help or contact a Poison Control Center (1-800-222-1222) right away.

DIRECTIONS

Adult and children 12 years and over:

- when practical, cleanse the affected area with mild soap and warm water and rinse thoroughly. Gently dry by patting or blotting with toilet tissue or a soft cloth before application of this product.
- apply externally to the affected area up to 6 times a day

children under 12 years of age: consult a doctor.

OTHER INFORMATION

Store between 15°-30° C (59°-30° F)

INACTIVE INGREDIENTS

Benzyl Alcohol, Carbomer 940, Cholesterol, Isopropyl Myristate, Lecithin (Soya), Polysorbate 80, Propylene Glycol, Purified Water, Triethanolamine, Vitamin-E Acetate

QUESTIONS

1-888-287-1915